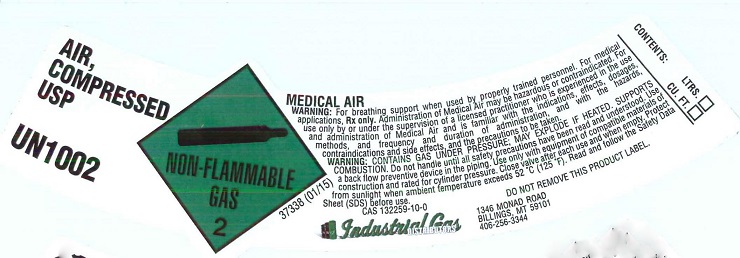 DRUG LABEL: Air
NDC: 55749-007 | Form: GAS
Manufacturer: Industrial Gas Distributors Inc
Category: prescription | Type: HUMAN PRESCRIPTION DRUG LABEL
Date: 20151214

ACTIVE INGREDIENTS: AIR 1000 mL/1 L

Air

PACKAGE LABEL

AIR, COMPRESSED USP UN1002
NON-FLAMMABLE GAS 2
MEDICAL AIR
WARNING: For breathing support when used by properly trained personnel. For medical applications, Rx only. Administration of Medical Air may be hazardous or contraindicated. For use only by or under the supervision of licensed practitioner who is experienced in the use and administration of Medical Air and is familiar with the indications, effects, dosages, methods, and frequency and duration of administration, and with the hazards, contraindications and side effects, and the precautions to be taken.
WARNING: CONTAINS GAS UNDER PRESSURE; MAY EXPLODE IF HEATED. SUPPORTS COMBUSTION. Do not handle until all safety precautions have been read and understood. Use a back flow preventive device in the piping. Use only with equipment of compatible materials of construction and rated for cylinder pressure. Close valve ager each use and when empty. Protect from sunlight when ambient temperature exceeds 52 degrees C (125 degrees F). Read and follow the Safety Data Sheet (SDS) before use.
CAS 132259-10-0 DO NOT REMOVE THIS PRODUCT LABEL
Industrial Gas DISTRIBUTORS 1346 MONAD ROAD BILLINGS, MT 59101 406-256-3344
CONTENTS: LTRS. CU.FT.